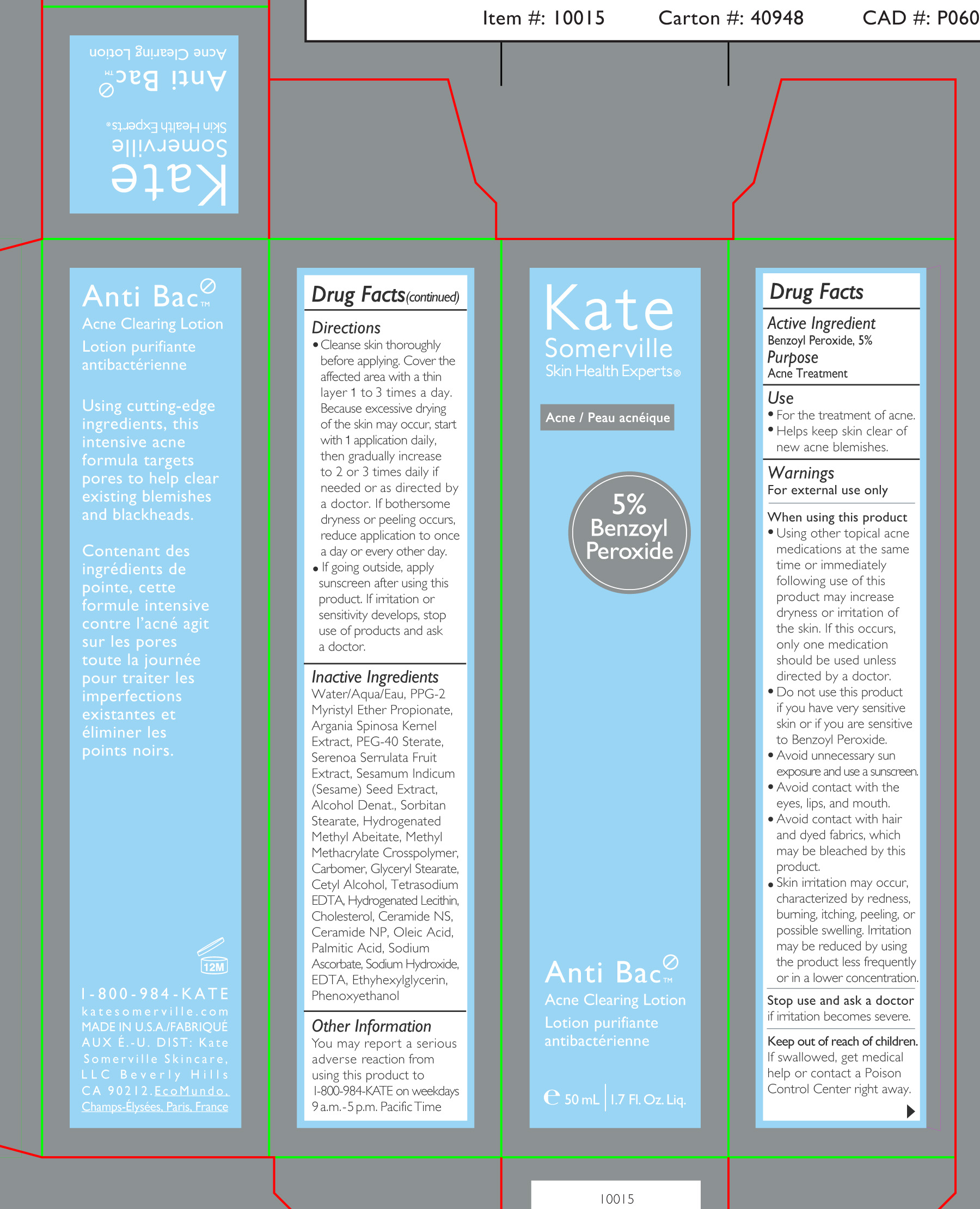 DRUG LABEL: Anti Bac Acne Clearing
NDC: 56152-4012 | Form: LOTION
Manufacturer: Cosmetic Enterprise Ltd
Category: otc | Type: HUMAN OTC DRUG LABEL
Date: 20251010

ACTIVE INGREDIENTS: BENZOYL PEROXIDE 5 g/100 mL
INACTIVE INGREDIENTS: METHYL METHACRYLATE/GLYCOL DIMETHACRYLATE CROSSPOLYMER; PEG-40 STEARATE; WATER; PPG-2 MYRISTYL ETHER PROPIONATE; SERENOA REPENS WHOLE; SESAME SEED; SODIUM ASCORBATE; SODIUM HYDROXIDE; EDETIC ACID; PHENOXYETHANOL; EDETATE SODIUM; ETHYLHEXYLGLYCERIN; SORBITAN MONOSTEARATE; HYDROGENATED METHYL ABIETATE; CARBOXYPOLYMETHYLENE; GLYCERYL MONOSTEARATE; CETYL ALCOHOL; HYDROGENATED SOYBEAN LECITHIN; CHOLESTEROL; CERAMIDE NS DILAURATE; CERAMIDE NP; OLEIC ACID; PALMITIC ACID

Anti Bac Clearing Lotion

Active Ingredient

Benzoyl Peroxide 5%

Purpose

Acne Treatment

Use

- For the treatment of acne
- Helps keep skin clear of new acne blemishes

Keep out of reach of children. If swallowed, get medical help or contact a Poison Control Center right away.

Stop use and ask a doctorif irritation becomes severe.

Warnings

For external use only

- When using this product
- Using other topical acne medications at the same time or immediately following use of this product may increase dryness or irritation of the skin. If this occurs, only one medication should be used unless directed by a doctor.
- Do not use this product if you have very sensitive skin or if you are sensitive to Benzoyl Peroxide.
- Avoid unnecesary sun exposure and use a sunscreen
- Avoid contact with the eyes, lips, and mouth.
- Avoid contact with hair and dyed fabrics, which may be bleached by this product
- Skin irritation may occur, characterized by redness, burning, itching, peeling, or possible swelling. Irritation may be reduced by using the product less frequently or in a lower concentration.

Directions

- Clease Skin thoroughly before applying. Cover the affected area with a thin layer 1 to 3 days. Because excessive drying of the skin may occur, start with 1 application daily, then gradually increase to 2 or 3 times daily if needed or as directed by a doctor by a doctor. If bothersome dryness or peeling occurs, reduce application to once a day or every other day.
- If going outside apply sunscreen after using this product. If irritation or sensitivity develops, stop use of products and ask a doctor.

Inactive Ingredients

Water/Aqua/Eau, PPG-2 Myristyl Ether Propionate, Argania Spinosa Kernel Extract, PEG-40 Sterate, Serenoa Serrulata Fruit Extract, Sesamum Indicum (sesame) Seed Extract, Alcohol Denat., Sorbitan Stearate, Hydrogenated Methyl Abeitate, Methyl Methacrylate Crosspolymer, Carbomer, Glyceryl Stearate, Cetyl Alcohol, Tetrasodium EDTA, Hydrogenated Lecithin, Cholesterol, Ceramide NS, Ceramide NP, Oleic Acid, Plamitic Acid, Sodium Ascorbate, Sodium Hydroxide, EDTA, Ethylhexylglycerin, Phenoxyethanol

PACKAGE LABEL

Kate Somerville

Acne/Peau acneique

5% Benzoyl Peroxide

Anti Bac

Acne Clearing Lotion

Lotion purifiante actibacterienne

50mL 1.7 Fl Oz Liq